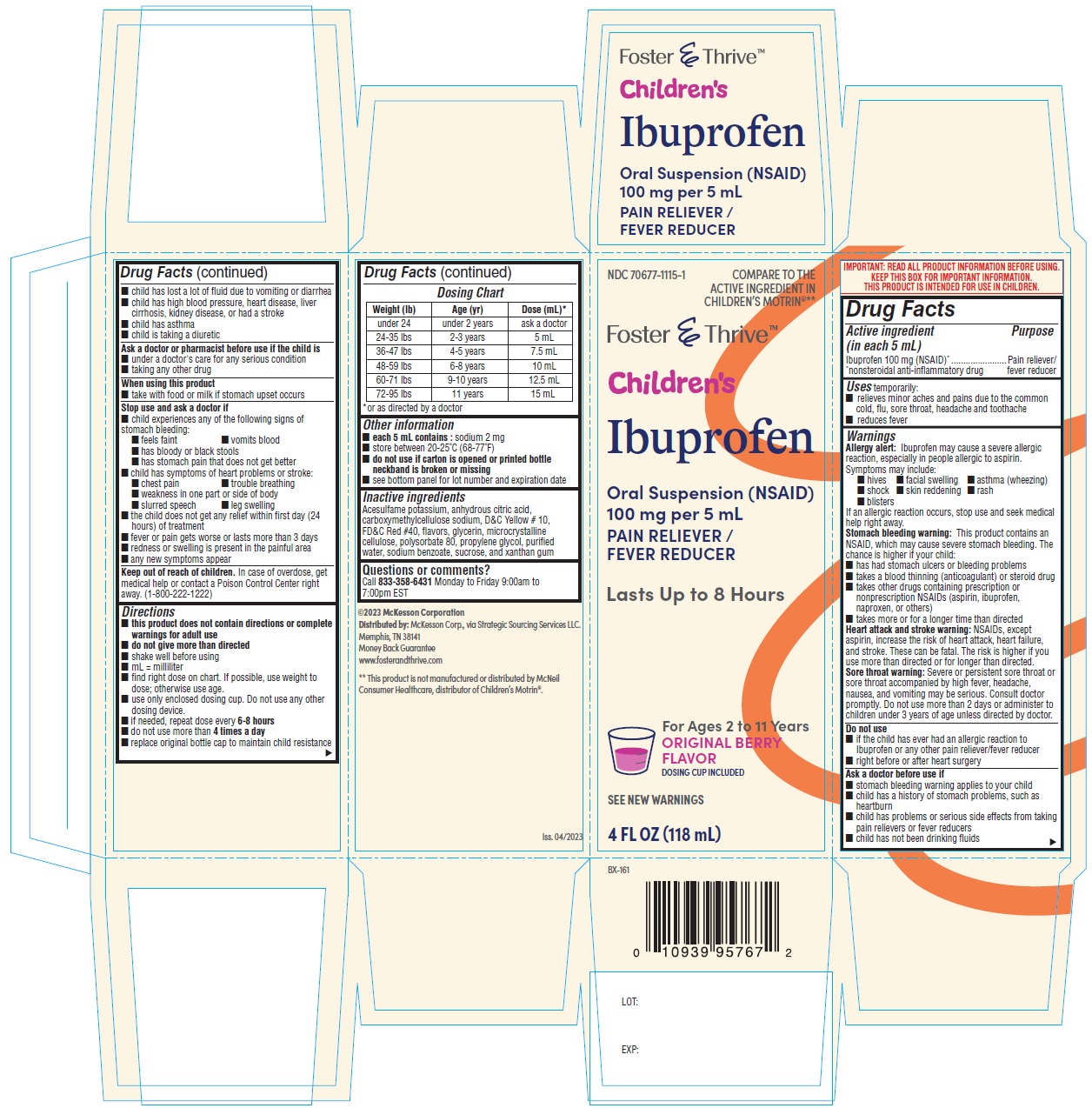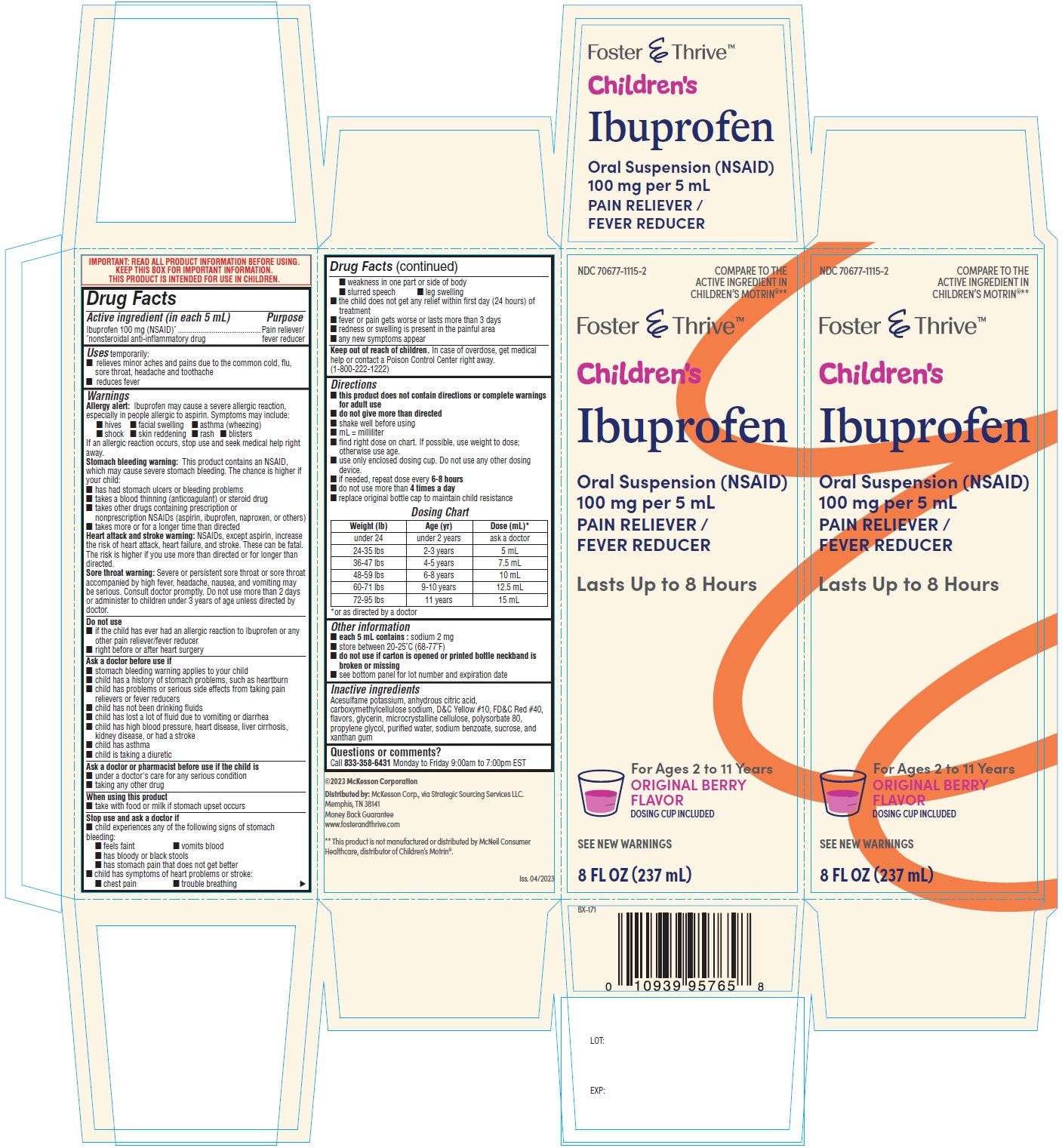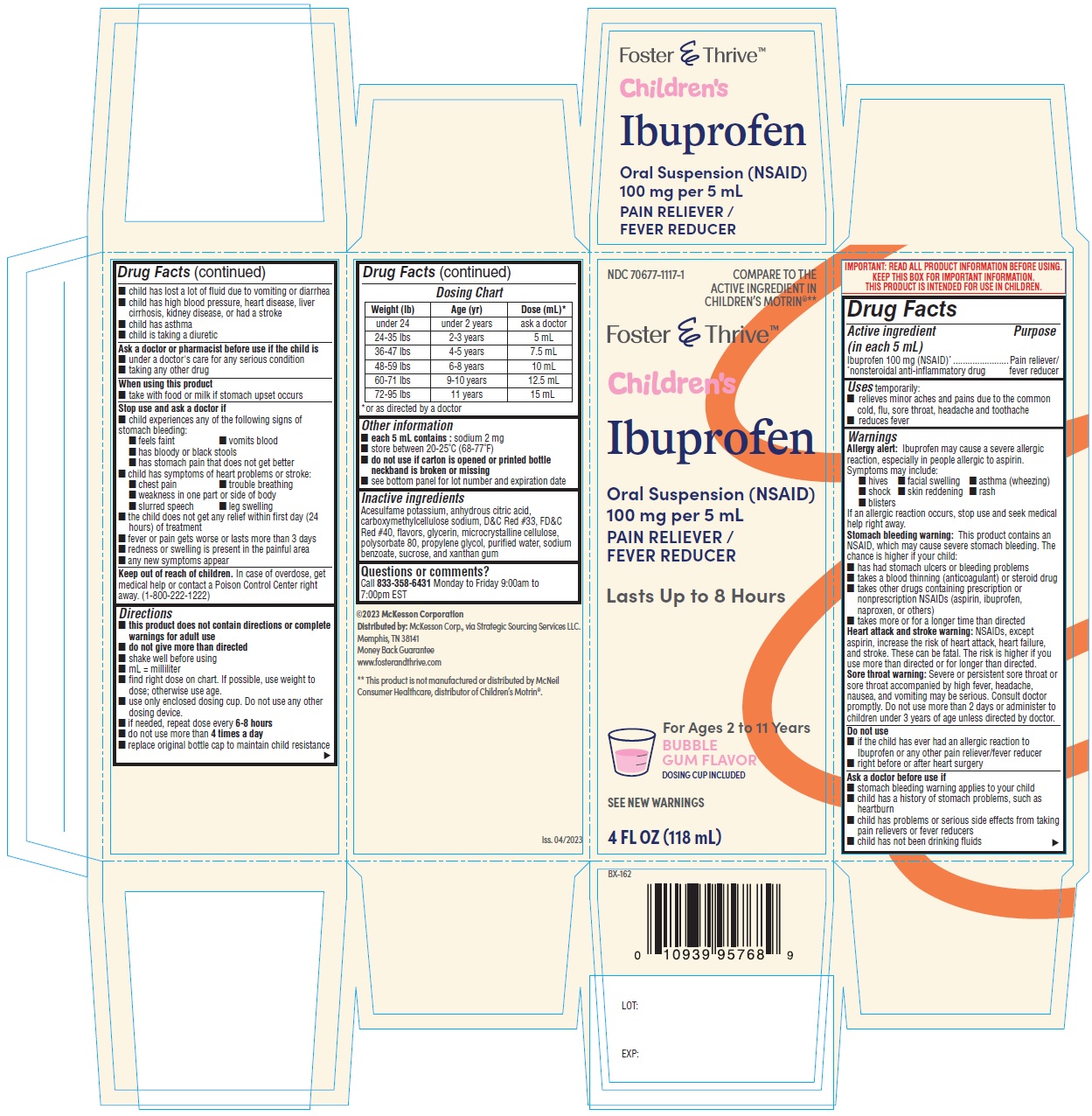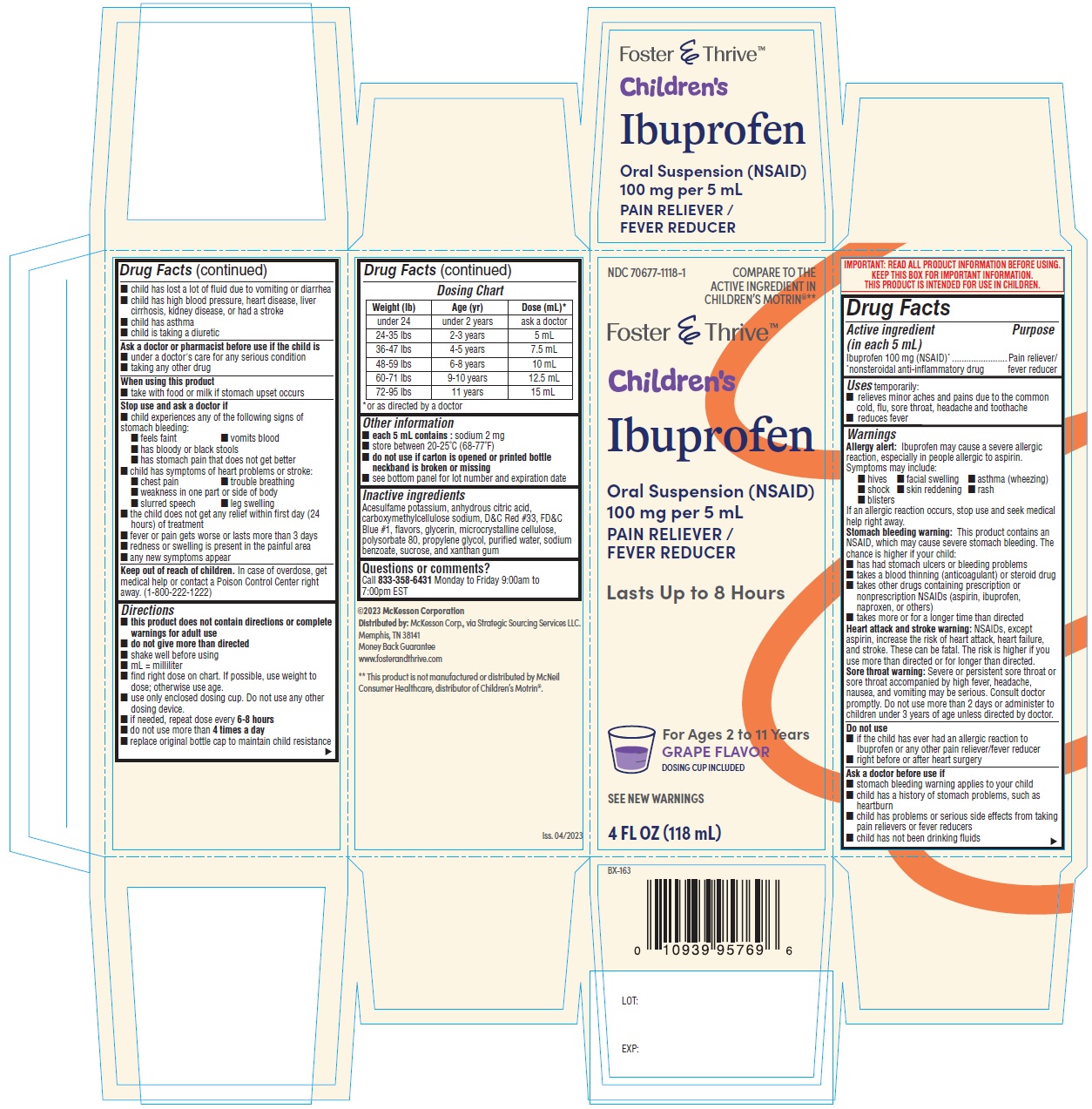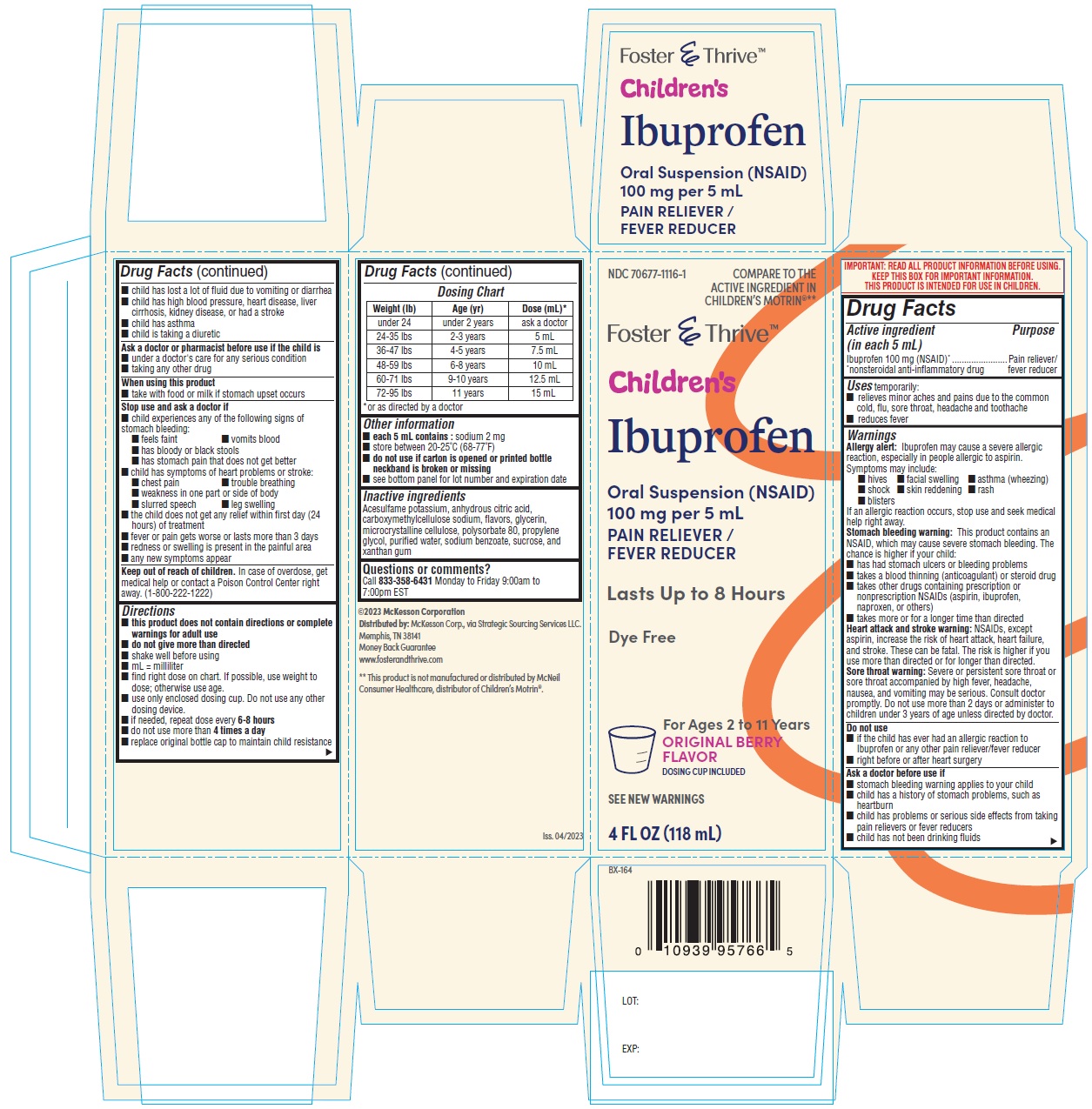 DRUG LABEL: Ibuprofen Oral
NDC: 70677-1115 | Form: SUSPENSION
Manufacturer: Strategic Sourcing Services
Category: otc | Type: Human OTC Drug Label
Date: 20250220

ACTIVE INGREDIENTS: IBUPROFEN 100 mg/5 mL
INACTIVE INGREDIENTS: ACESULFAME POTASSIUM; ANHYDROUS CITRIC ACID; CARBOXYMETHYLCELLULOSE SODIUM; D&C YELLOW NO. 10; GLYCERIN; FD&C RED NO. 40; CELLULOSE, MICROCRYSTALLINE; POLYSORBATE 80; PROPYLENE GLYCOL; WATER; SODIUM BENZOATE; SUCROSE; XANTHAN GUM

Ibuprofen Oral Suspension USP, 100 mg/5 mL (OTC)

ACTIVE INGREDIENT(S)

Ibuprofen 100 mg (NSAID)*
*nonsteroidal anti-inflammatory drug

PURPOSE

Pain reliever/ fever reducer

USE(S)

temporarily:
■ relieves minor aches and pains due to the common cold, flu, sore throat, headache and toothache
■ reduces fever

WARNINGS

Allergy alert: Ibuprofen may cause a severe allergic reaction, especially in people allergic to aspirin.
Symptoms may include:
■ hives ■ facial swelling ■ asthma (wheezing)
■ shock ■ skin reddening ■ rash
■ blisters
If an allergic reaction occurs, stop use and seek medical help right away.
Stomach bleeding warning: This product contains an NSAID, which may cause severe stomach bleeding. The chance is higher if your child:
■ has had stomach ulcers or bleeding problems
■ takes a blood thinning (anticoagulant) or steroid drug
■ takes other drugs containing prescription or nonprescription NSAIDs (aspirin, ibuprofen, naproxen, or others)
■ takes more or for a longer time than directed
Heart attack and stroke warning: NSAIDs, except aspirin, increase the risk of heart attack, heart failure, and stroke. These can be fatal. The risk is higher if you use more than directed or for longer than directed.
Sore throat warning: Severe or persistent sore throat or sore throat accompanied by high fever, headache, nausea, and vomiting may be serious. Consult doctor promptly. Do not use more than 2 days or administer to children under 3 years of age unless directed by doctor.

DO NOT USE

■ if the child has ever had an allergic reaction to Ibuprofen or any other pain reliever/fever reducer
■ right before or after heart surgery

ASK A DOCTOR BEFORE USE IF

■ stomach bleeding warning applies to your child
■ child has a history of stomach problems, such as heartburn
■ child has problems or serious side effects from taking pain relievers or fever reducers
■ child has not been drinking fluids
■ child has lost a lot of fluid due to vomiting or diarrhea
■ child has high blood pressure, heart disease, liver cirrhosis, kidney disease, or had a stroke
■ child has asthma
■ child is taking a diuretic

ASK A DOCTOR OR PHARMACIST BEFORE USE IF

■ under a doctor's care for any serious condition
■ taking any other drug

WHEN USING THIS PRODUCT

■ take with food or milk if stomach upset occurs

STOP USE AND ASK DOCTOR IF

■ child experiences any of the following signs of stomach bleeding:
■ feels faint ■ vomits blood
■ has bloody or black stools
■ has stomach pain that does not get better
■ child has symptoms of heart problems or stroke:
■ chest pain ■ trouble breathing
■ weakness in one part or side of body
■ slurred speech ■ leg swelling
■ the child does not get any relief within first day (24 hours) of treatment
■ fever or pain gets worse or lasts more than 3 days
■ redness or swelling is present in the painful area
■ any new symptoms appear

Keep out of reach of children. In case of overdose, get medical help or contact a Poison Control Center right away. (1-800-222-1222)

DIRECTIONS

■ this product does not contain directions or complete warnings for adult use
■ do not give more than directed
■ shake well before using
■ mL = milliliter
■ find right dose on chart. If possible, use weight to dose; otherwise use age.
■ use only enclosed dosing cup. Do not use any other dosing device.
■ if needed, repeat dose every 6-8 hours
■ do not use more than 4 times a day
■ replace original bottle cap to maintain child resistance

Dosing Chart

Weight (lb) Age (yr) Dose (mL)* | Weight (lb) Age (yr) Dose (mL)* | Weight (lb) Age (yr) Dose (mL)*
under 24 under 2 years ask a doctor | under 24 under 2 years ask a doctor | under 24 under 2 years ask a doctor
24-35 lbs 2-3 years 5 mL | 24-35 lbs 2-3 years 5 mL | 24-35 lbs 2-3 years 5 mL
36-47 lbs 4-5 years 7.5 mL | 36-47 lbs 4-5 years 7.5 mL | 36-47 lbs 4-5 years 7.5 mL
48-59 lbs 6-8 years 10 mL | 48-59 lbs 6-8 years 10 mL | 48-59 lbs 6-8 years 10 mL
60-71 lbs 9-10 years 12.5 mL | 60-71 lbs 9-10 years 12.5 mL | 60-71 lbs 9-10 years 12.5 mL
72-95 lbs 11 years 15 mL | 72-95 lbs 11 years 15 mL | 72-95 lbs 11 years 15 mL

*or as directed by a doctor

OTHER INFORMATION

■ each 5 mL contains : sodium 2 mg
■ store between 20-25°C (68-77°F)
■ do not use if carton is opened or printed bottle neckband is broken or missing
■ see bottom panel for lot number and expiration date

INACTIVE INGREDIENT

Acesulfame potassium, anhydrous citric acid, carboxymethylcellulose sodium, D&C Yellow # 10, FD&C Red #40, flavors, glycerin, microcrystalline cellulose, polysorbate 80, propylene glycol, purified water, sodium benzoate, sucrose, and xanthan gum

QUESTIONS or COMMENTS?

Call 833-358-6431 Monday to Friday 9:00am to 7:00pm EST

©2023 McKesson Corporation
Distributed by: McKesson Corp., via Strategic Sourcing Services LLC.
Memphis, TN 38141
Money Back Guarantee
www.fosterandthrive.com
** This product is not manufactured or distributed by McNeil
Consumer Healthcare, distributor of Children’s Motrin®.

PRINCIPAL DISPLAY PANEL

ibuprofen-oral-suspension-berry-flavor-container-carton-118 mL

ibuprofen-oral-suspension-berry-original-flavor-container-carton-237 mL

ibuprofen-oral-suspension-bubble-gum-flavor-container-carton-118 mL

ibuprofen-oral-suspension-grape-flavor-container-carton-118 mL

ibuprofen-oral-suspension-original-berry-flavor-container-carton-118 mL